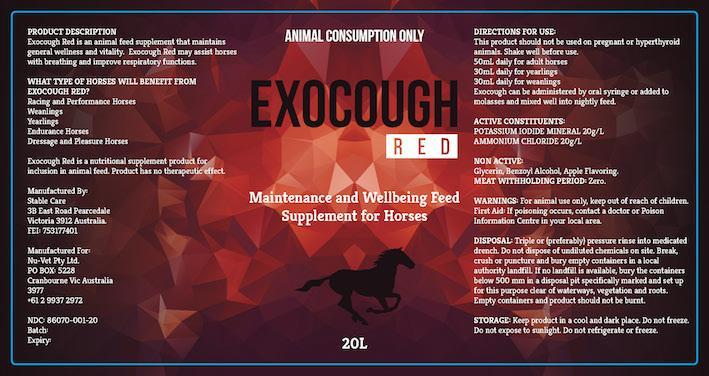 DRUG LABEL: Exocough
NDC: 86070-001 | Form: SOLUTION
Manufacturer: Nu-Vet Pty Ltd
Category: animal | Type: OTC ANIMAL DRUG LABEL
Date: 20160825

ACTIVE INGREDIENTS: POTASSIUM IODIDE 20 g/1 L; AMMONIUM CHLORIDE 20 g/1 L
INACTIVE INGREDIENTS: GLYCERIN; WATER; BENZYL ALCOHOL

Active

POTASSIUM IODIDE 20 g / L
AMMONIUM CHLORIDE 20 g /L

Inactive ingrdients

Glycerin, H20 Distilled Water, Benzoyl Alcohol and Red Dye

Purpose of use

Equine Health Supplement

Do not use

Not to be used for horses in human consumption.